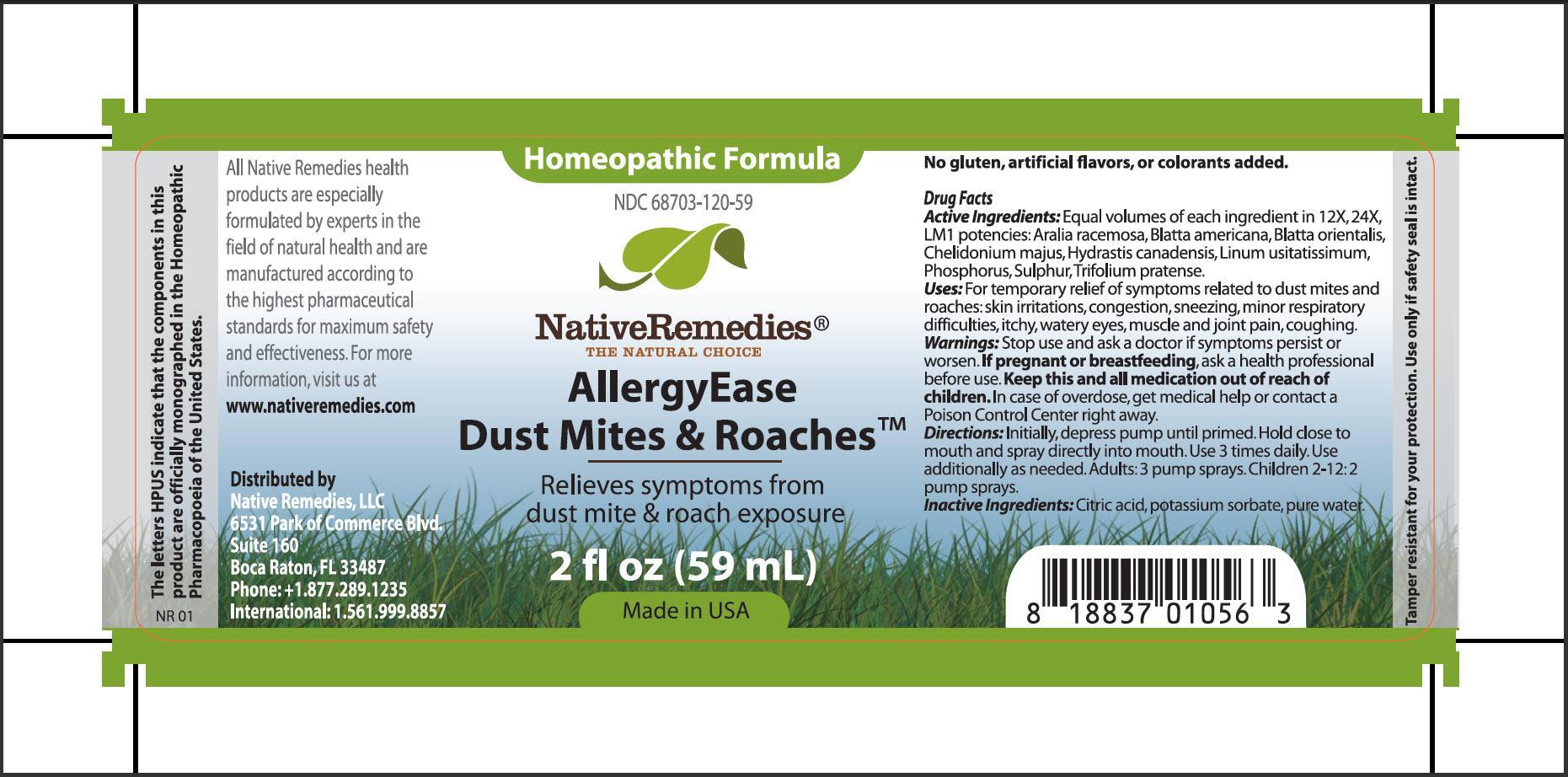 DRUG LABEL: AllergyEase Dust Mites and Roaches
NDC: 68703-120 | Form: SPRAY
Manufacturer: Native Remedies, LLC
Category: homeopathic | Type: HUMAN OTC DRUG LABEL
Date: 20130703

ACTIVE INGREDIENTS: ARALIA RACEMOSA ROOT 12 [hp_X]/59 mL; PERIPLANETA AMERICANA 12 [hp_X]/59 mL; BLATTA ORIENTALIS 12 [hp_X]/59 mL; CHELIDONIUM MAJUS 12 [hp_X]/59 mL; GOLDENSEAL 12 [hp_X]/59 mL; FLAX SEED 12 [hp_X]/59 mL; PHOSPHORUS 12 [hp_X]/59 mL; SULFUR 12 [hp_X]/59 mL; TRIFOLIUM PRATENSE FLOWER 12 [hp_X]/59 mL
INACTIVE INGREDIENTS: CITRIC ACID MONOHYDRATE; POTASSIUM SORBATE; WATER

AllergyEase Dust Mites and Roaches

PURPOSE

Relieves symptoms from dust mite and roaches exposure

Drug Facts
Active Ingredients: Equal volumes of each ingredient in 12X, 24X, LM1 potencies. Aralia racemosa, Blatta americana, Blatta orientalis, Chelidonium majus, Hydrastis canadensis, Linum usitatissimum, Phosphorus, Sulphur, Trifolium pratense

INDICATIONS AND USAGE

Uses: For temporary relief of symptoms related to dust mites and roaches: skin irritations, congestion, sneezing, minor respiratory difficulties, itchy, watery eyes, muscle and join pain, coughing

WARNINGS

Warnings: Stop use and ask a doctor if symptoms persist or worsen

PREGNANCY OR BREAST FEEDING

If pregnant of breastfeeding, ask a health professional before use

KEEP OUT OF REACH OF CHILDREN

Keep this and all medication out of reach of children

OVERDOSAGE

In case of overdose, get medical help or contact a Poison Control Center right away

DOSAGE AND ADMINISTRATION

Directions: Initially, depress pump until primed. Hold close to mouth and spray directly into mouth. Use 3 times daily. Use additionally as needed. Adults: 3 pump sprays. Children 2-12: 2 pump sprays

Inactive Ingredients: Citric acid, potassium sorbate, pure water

PATIENT COUNSELING INFORMATION

The letter HPUS indicate that the components in this product are officially monographed in the Homeopathic Pharmacopoeia of the United States

All Native Remedies health products are especially formulated by experts in the field of natural health and are manufactured according to the highest pharmaceutical standards for maximum safety and effectiveness. For more information, visit us at www.nativeremedies.com

Distributed by
Native Remedies, LLC
6531 Park of Commerce Blvd.
Suite 160
Boca Raton, FL 33487
Phone: +1.877.289.1235
International: 1.561.999.8857

No gluten, artificial flavors, or colorants added

STORAGE AND HANDLING

Tamper resistant for your protection. Use only if safety seal is intact